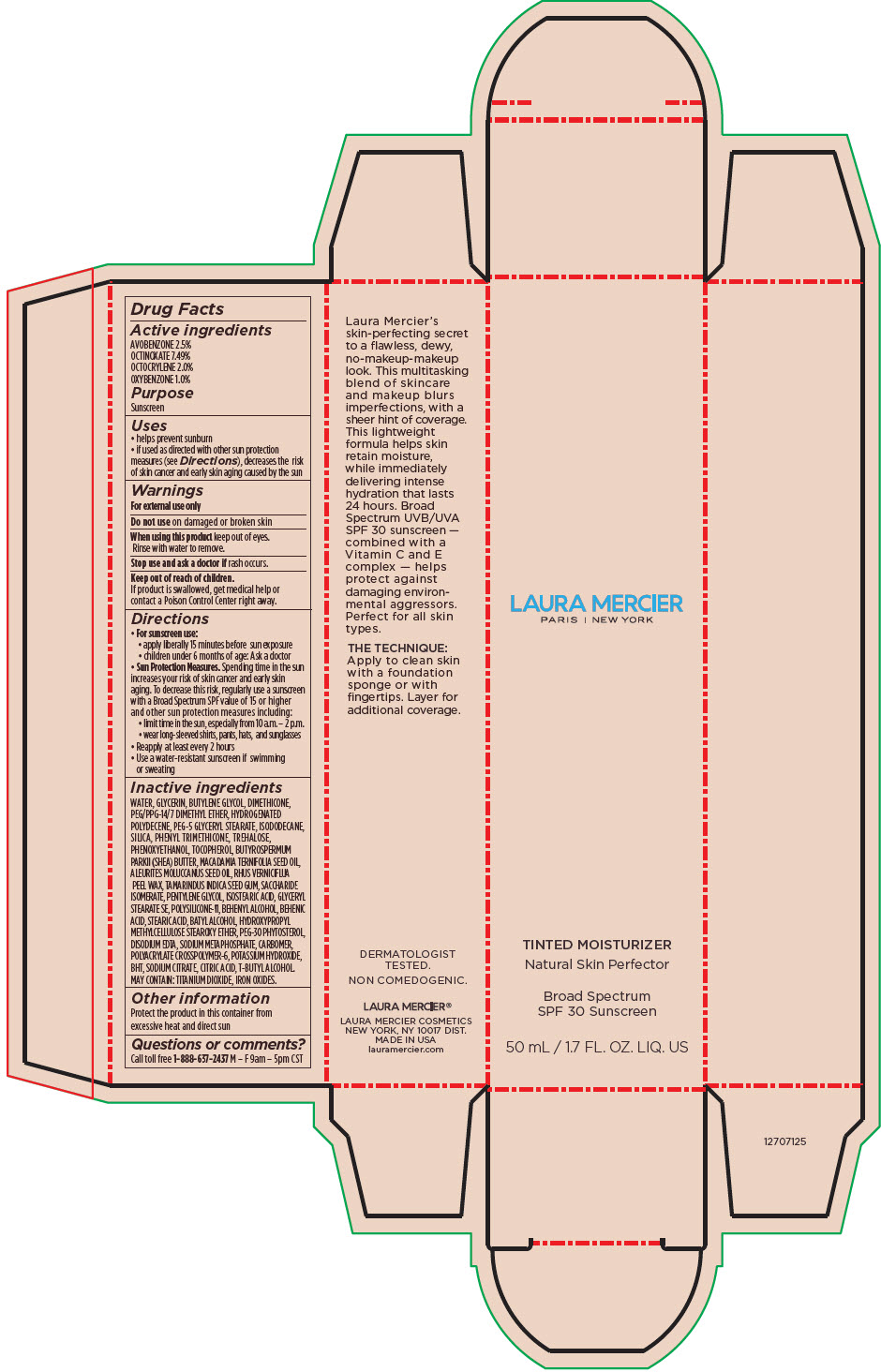 DRUG LABEL: Laura Mercier Tinted Moisturizer Natural Skin Perfector Broad Spectrum SPF 30 Sunscreen
NDC: 82761-035 | Form: CREAM
Manufacturer: Laura Mercier US Buyer LLC
Category: otc | Type: HUMAN OTC DRUG LABEL
Date: 20231004

ACTIVE INGREDIENTS: AVOBENZONE 1.25 g/50 mL; OCTINOXATE 3.745 g/50 mL; OCTOCRYLENE 1 g/50 mL; OXYBENZONE 0.5 g/50 mL
INACTIVE INGREDIENTS: WATER; GLYCERIN; BUTYLENE GLYCOL; DIMETHICONE; PEG/PPG-14/7 DIMETHYL ETHER; HYDROGENATED POLYDECENE TYPE I; PEG-5 GLYCERYL STEARATE; ISODODECANE; SILICON DIOXIDE; PHENYL TRIMETHICONE; TREHALOSE; PHENOXYETHANOL; .ALPHA.-TOCOPHEROL; SHEA BUTTER; MACADAMIA OIL; KUKUI NUT OIL; TOXICODENDRON VERNICIFLUUM FRUIT RIND WAX; SACCHARIDE ISOMERATE; PENTYLENE GLYCOL; ISOSTEARIC ACID; GLYCERYL MONOSTEARATE; DIMETHICONE/VINYL DIMETHICONE CROSSPOLYMER (SOFT PARTICLE); DOCOSANOL; BEHENIC ACID; STEARIC ACID; BATILOL; EDETATE DISODIUM; SODIUM POLYMETAPHOSPHATE; CARBOMER HOMOPOLYMER, UNSPECIFIED TYPE; AMMONIUM ACRYLOYLDIMETHYLTAURATE, DIMETHYLACRYLAMIDE, LAURYL METHACRYLATE AND LAURETH-4 METHACRYLATE COPOLYMER, TRIMETHYLOLPROPANE TRIACRYLATE CROSSLINKED (45000 MPA.S); POTASSIUM HYDROXIDE; BUTYLATED HYDROXYTOLUENE; SODIUM CITRATE, UNSPECIFIED FORM; CITRIC ACID MONOHYDRATE; TERT-BUTYL ALCOHOL; FERRIC OXIDE RED; FERRIC OXIDE YELLOW; FERROSOFERRIC OXIDE; TITANIUM DIOXIDE

Laura Mercier Tinted Moisturizer Natural Skin Perfector Broad Spectrum SPF 30 Sunscreen

Drug Facts

Active ingredients

AVOBENZONE 2.5%

OCTINOXATE 7.49%

OCTOCRYLENE 2.0%

OXYBENZONE 1.0%

Purpose

Sunscreen

Uses

- helps prevent sunburn
- if used as directed with other sun protection measures (see Directions), decreases the risk of skin cancer and early skin aging caused by the sun

Warnings

For external use only

Do not use on damaged or broken skin

When using this product keep out of eyes. Rinse with water to remove.

Stop use and ask a doctor if rash occurs.

Keep out of reach of children.

If product is swallowed, get medical help or contact a Poison Control Center right away.

Directions

- For sunscreen use:
  - apply liberally 15 minutes before sun exposure
  - children under 6 months of age: Ask a doctor
- Sun Protection Measures. Spending time in the sun increases your risk of skin cancer and early skin aging. To decrease this risk, regularly use a sunscreen with a Broad Spectrum SPF value of 15 or higher and other sun protection measures including:
  - limit time in the sun, especially from 10 a.m. – 2 p.m.
  - wear long-sleeved shirts, pants, hats, and sunglasses
- Reapply at least every 2 hours
- Use a water-resistant sunscreen if swimming or sweating

Inactive ingredients

WATER, GLYCERIN, BUTYLENE GLYCOL, DIMETHICONE, PEG/PPG-14/7 DIMETHYL ETHER, HYDROGENATED POLYDECENE, PEG-5 GLYCERYL STEARATE, ISODODECANE, SILICA, PHENYL TRIMETHICONE, TREHALOSE, PHENOXYETHANOL, TOCOPHEROL, BUTYROSPERMUM PARKII (SHEA) BUTTER, MACADAMIA TERNIFOLIA SEED OIL, ALEURITES MOLUCCANUS SEED OIL, RHUS VERNICIFLUA PEEL WAX, TAMARINDUS INDICA SEED GUM, SACCHARIDE ISOMERATE, PENTYLENE GLYCOL, ISOSTEARIC ACID, GLYCERYL STEARATE SE, POLYSILICONE-11, BEHENYL ALCOHOL, BEHENIC ACID, STEARIC ACID, BATYL ALCOHOL, HYDROXYPROPYL METHYLCELLULOSE STEAROXY ETHER, PEG-30 PHYTOSTEROL, DISODIUM EDTA, SODIUM METAPHOSPHATE, CARBOMER, POLYACRYLATE CROSSPOLYMER-6, POTASSIUM HYDROXIDE, BHT, SODIUM CITRATE, CITRIC ACID, T-BUTYL ALCOHOL. MAY CONTAIN: TITANIUM DIOXIDE, IRON OXIDES.

Other information

Protect the product in this container from excessive heat and direct sun

Questions or comments?

Call toll free 1-888-637-2437 M – F 9am – 5pm CST

PRINCIPAL DISPLAY PANEL - 50 mL Tube Carton - 0N1 - Petal

LAURA MERCIER
PARIS | NEW YORK

TINTED MOISTURIZER
Natural Skin Perfector

Broad Spectrum
SPF 30 Sunscreen

50 mL / 1.7 FL. OZ. LIQ. US

PRINCIPAL DISPLAY PANEL - 50 mL Tube Carton - 0W1 - Pearl

LAURA MERCIER
PARIS | NEW YORK

TINTED MOISTURIZER
Natural Skin Perfector

Broad Spectrum
SPF 30 Sunscreen

50 mL / 1.7 FL. OZ. LIQ. US

PRINCIPAL DISPLAY PANEL - 50 mL Tube Carton - 1C0 - Cameo

LAURA MERCIER
PARIS | NEW YORK

TINTED MOISTURIZER
Natural Skin Perfector

Broad Spectrum
SPF 30 Sunscreen

50 mL / 1.7 FL. OZ. LIQ. US

PRINCIPAL DISPLAY PANEL - 50 mL Tube Carton - 1N2 - Vanille

LAURA MERCIER
PARIS | NEW YORK

TINTED MOISTURIZER
Natural Skin Perfector

Broad Spectrum
SPF 30 Sunscreen

50 mL / 1.7 FL. OZ. LIQ. US

PRINCIPAL DISPLAY PANEL - 50 mL Tube Carton - 1W1 - Porcelain

LAURA MERCIER
PARIS | NEW YORK

TINTED MOISTURIZER
Natural Skin Perfector

Broad Spectrum
SPF 30 Sunscreen

50 mL / 1.7 FL. OZ. LIQ. US

PRINCIPAL DISPLAY PANEL - 50 mL Tube Carton - 2C1 - Blush

LAURA MERCIER
PARIS | NEW YORK

TINTED MOISTURIZER
Natural Skin Perfector

Broad Spectrum
SPF 30 Sunscreen

50 mL / 1.7 FL. OZ. LIQ. US

PRINCIPAL DISPLAY PANEL - 50 mL Tube Carton - 2N1 - Nude

LAURA MERCIER
PARIS | NEW YORK

TINTED MOISTURIZER
Natural Skin Perfector

Broad Spectrum
SPF 30 Sunscreen

50 mL / 1.7 FL. OZ. LIQ. US

PRINCIPAL DISPLAY PANEL - 50 mL Tube Carton - 2W1 - Natural

LAURA MERCIER
PARIS | NEW YORK

TINTED MOISTURIZER
Natural Skin Perfector

Broad Spectrum
SPF 30 Sunscreen

50 mL / 1.7 FL. OZ. LIQ. US

PRINCIPAL DISPLAY PANEL - 50 mL Tube Carton - 3C1 - Fawn

LAURA MERCIER
PARIS | NEW YORK

TINTED MOISTURIZER
Natural Skin Perfector

Broad Spectrum
SPF 30 Sunscreen

50 mL / 1.7 FL. OZ. LIQ. US

PRINCIPAL DISPLAY PANEL - 50 mL Tube Carton - 3N1 - Sand

LAURA MERCIER
PARIS | NEW YORK

TINTED MOISTURIZER
Natural Skin Perfector

Broad Spectrum
SPF 30 Sunscreen

50 mL / 1.7 FL. OZ. LIQ. US

PRINCIPAL DISPLAY PANEL - 50 mL Tube Carton - 3W1 - Bisque

LAURA MERCIER
PARIS | NEW YORK

TINTED MOISTURIZER
Natural Skin Perfector

Broad Spectrum
SPF 30 Sunscreen

50 mL / 1.7 FL. OZ. LIQ. US

PRINCIPAL DISPLAY PANEL - 50 mL Tube Carton - 4C1 - Almond

LAURA MERCIER
PARIS | NEW YORK

TINTED MOISTURIZER
Natural Skin Perfector

Broad Spectrum
SPF 30 Sunscreen

50 mL / 1.7 FL. OZ. LIQ. US

PRINCIPAL DISPLAY PANEL - 50 mL Tube Carton - 4N1 - Wheat

LAURA MERCIER
PARIS | NEW YORK

TINTED MOISTURIZER
Natural Skin Perfector

Broad Spectrum
SPF 30 Sunscreen

50 mL / 1.7 FL. OZ. LIQ. US

PRINCIPAL DISPLAY PANEL - 50 mL Tube Carton - 4W1 - Tawny

LAURA MERCIER
PARIS | NEW YORK

TINTED MOISTURIZER
Natural Skin Perfector

Broad Spectrum
SPF 30 Sunscreen

50 mL / 1.7 FL. OZ. LIQ. US

PRINCIPAL DISPLAY PANEL - 50 mL Tube Carton - 5C1 - Nutmeg

LAURA MERCIER
PARIS | NEW YORK

TINTED MOISTURIZER
Natural Skin Perfector

Broad Spectrum
SPF 30 Sunscreen

50 mL / 1.7 FL. OZ. LIQ. US

PRINCIPAL DISPLAY PANEL - 50 mL Tube Carton - 5N1 - Walnut

LAURA MERCIER
PARIS | NEW YORK

TINTED MOISTURIZER
Natural Skin Perfector

Broad Spectrum
SPF 30 Sunscreen

50 mL / 1.7 FL. OZ. LIQ. US

PRINCIPAL DISPLAY PANEL - 50 mL Tube Carton - 5W1 - Tan

LAURA MERCIER
PARIS | NEW YORK

TINTED MOISTURIZER
Natural Skin Perfector

Broad Spectrum
SPF 30 Sunscreen

50 mL / 1.7 FL. OZ. LIQ. US

PRINCIPAL DISPLAY PANEL - 50 mL Tube Carton - 6C1 - Cacao

LAURA MERCIER
PARIS | NEW YORK

TINTED MOISTURIZER
Natural Skin Perfector

Broad Spectrum
SPF 30 Sunscreen

50 mL / 1.7 FL. OZ. LIQ. US

PRINCIPAL DISPLAY PANEL - 50 mL Tube Carton - 6W1 - Ganache

LAURA MERCIER
PARIS | NEW YORK

TINTED MOISTURIZER
Natural Skin Perfector

Broad Spectrum
SPF 30 Sunscreen

50 mL / 1.7 FL. OZ. LIQ. US

PRINCIPAL DISPLAY PANEL - 50 mL Tube Carton - 6N1 - Mocha

LAURA MERCIER
PARIS | NEW YORK

TINTED MOISTURIZER
Natural Skin Perfector

Broad Spectrum
SPF 30 Sunscreen

50 mL / 1.7 FL. OZ. LIQ. US